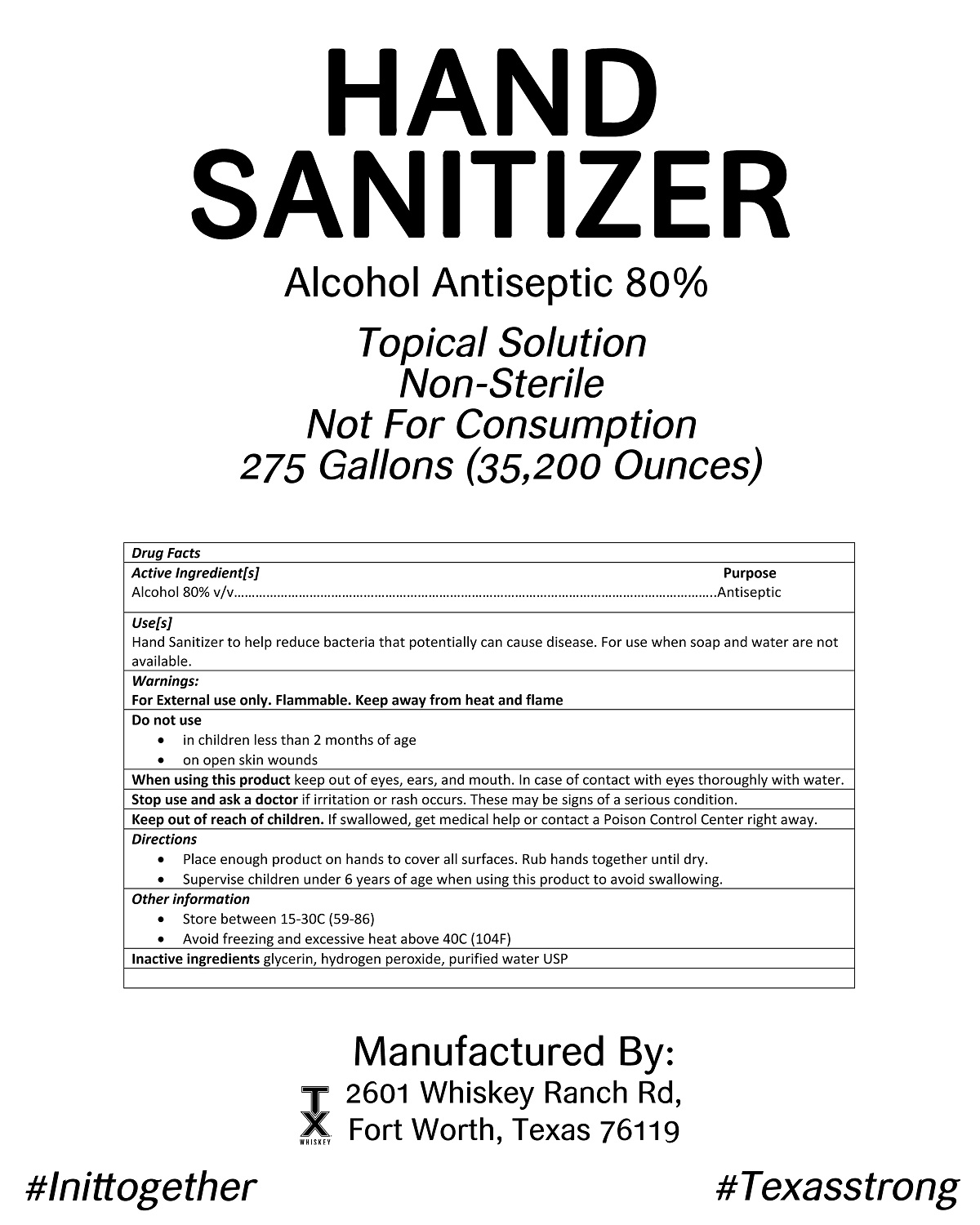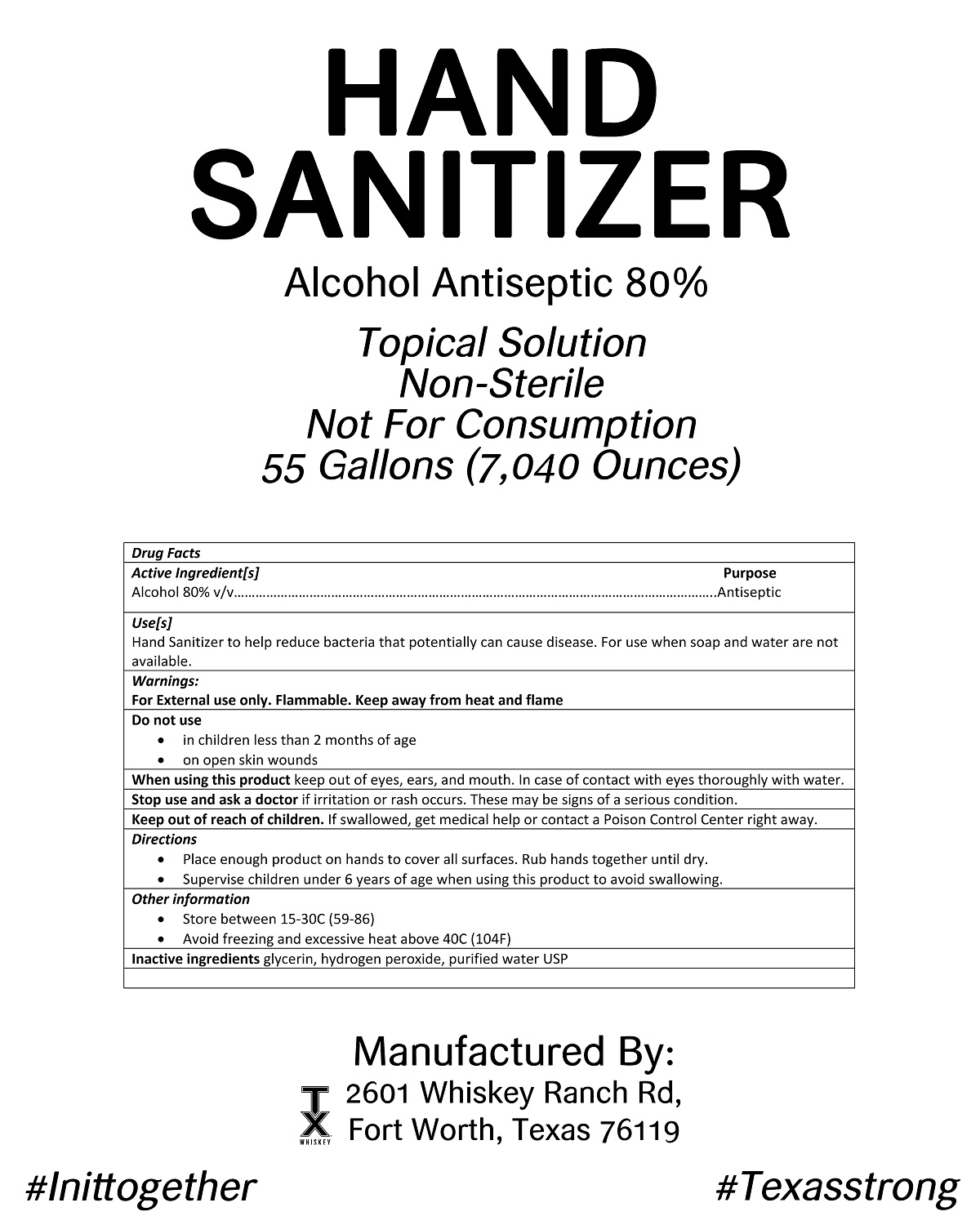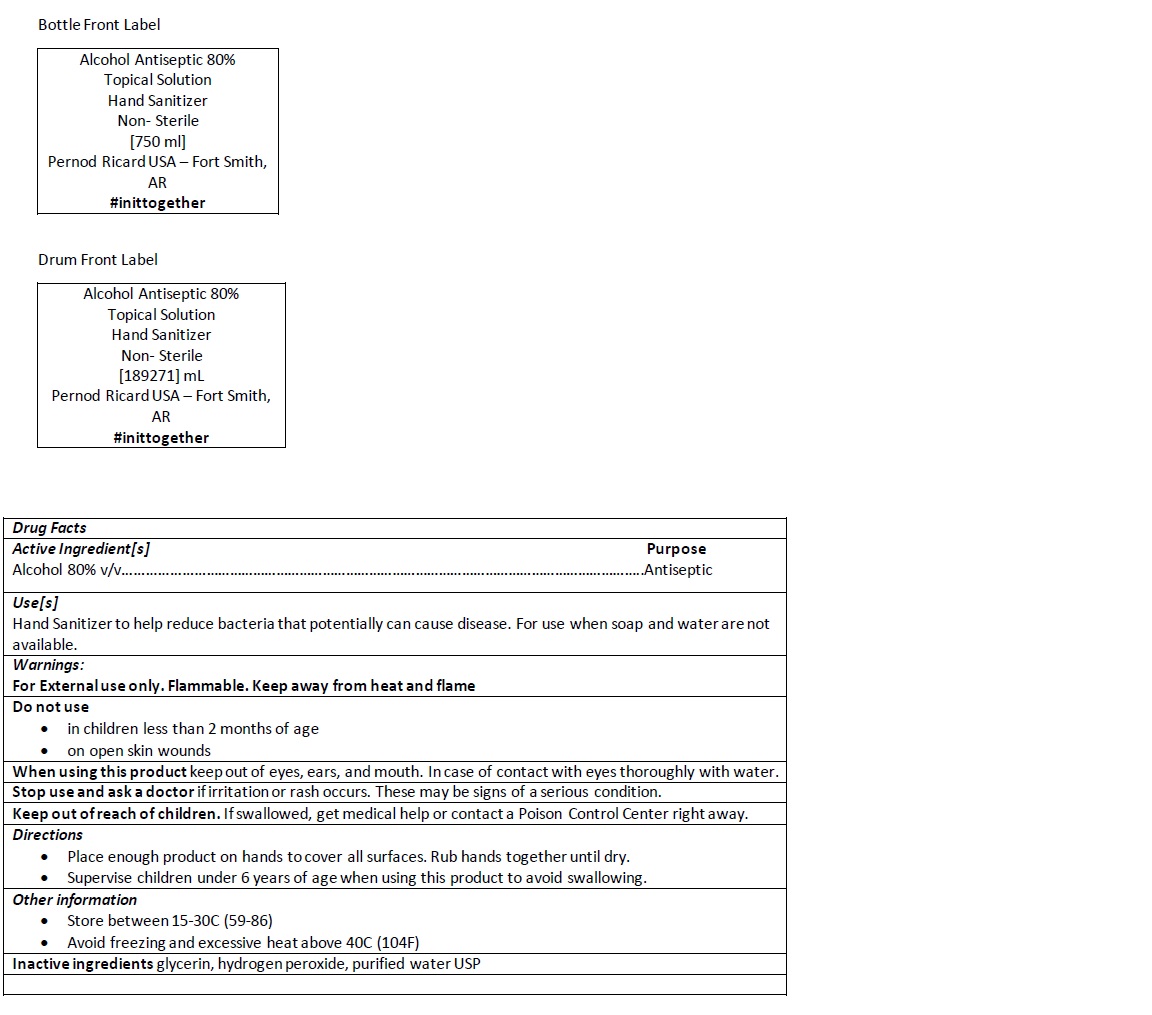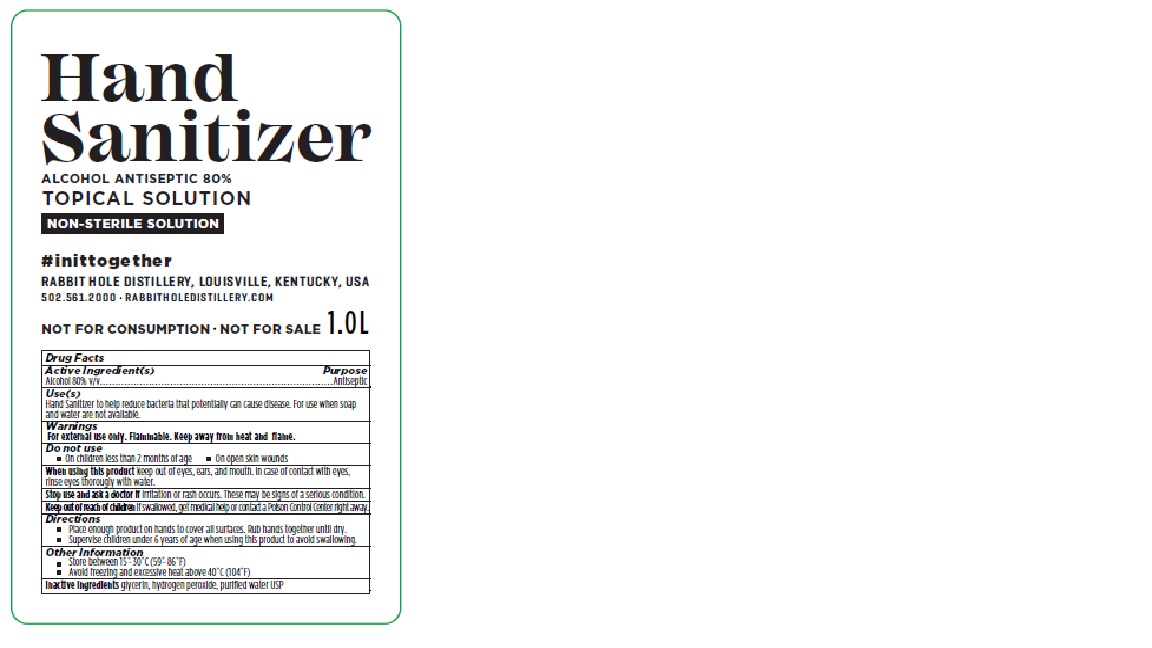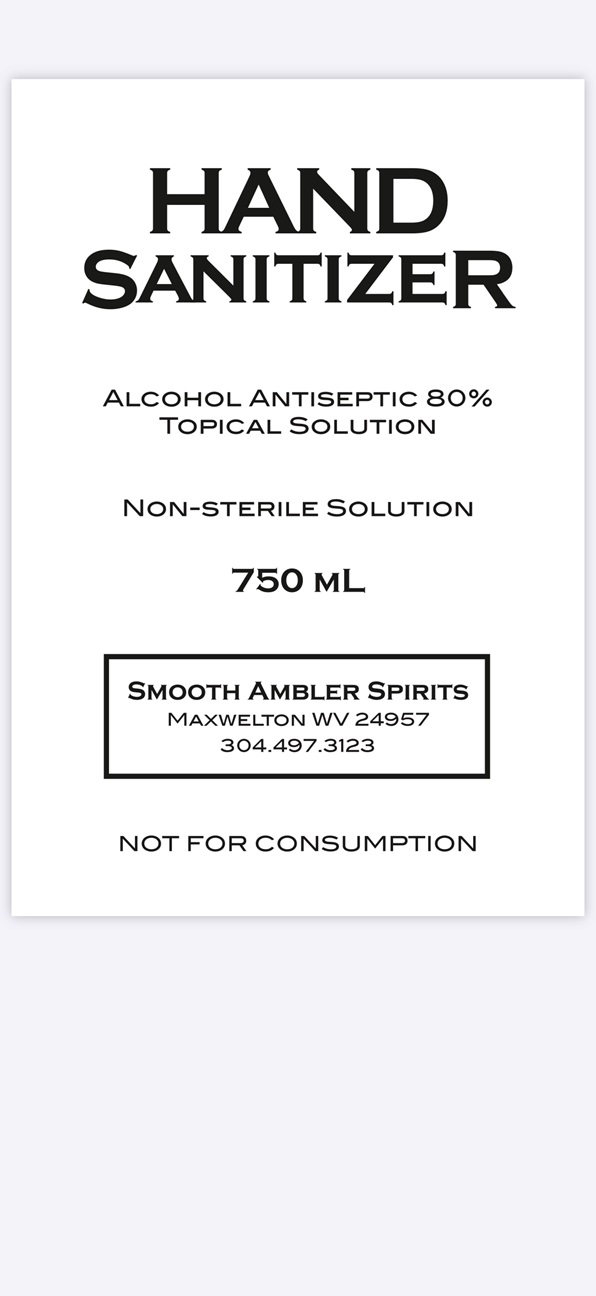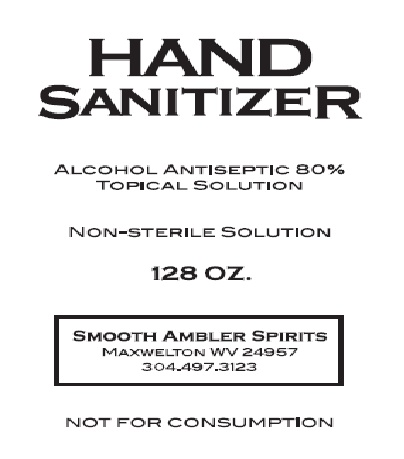 DRUG LABEL: hand sanitizer
NDC: 73785-001 | Form: SOLUTION
Manufacturer: Pernod Ricard USA
Category: otc | Type: HUMAN OTC DRUG LABEL
Date: 20200414

ACTIVE INGREDIENTS: ALCOHOL 8 mL/10 mL
INACTIVE INGREDIENTS: HYDROGEN PEROXIDE; WATER; GLYCERIN

Pernod Ricard Hand sanitizer

Active Ingredient[s] Purpose

Alcohol 80% v/v ................................. Anitseptic

Warnings:

For External use only. Flammable. Keep away from heat and flame

Do not use

- in children less than 2 months of age
- on open skin wounds

When using this product keep out of eyes, ears, and mounth. In case of contact with eyes flush thoroughly with water.

Stop use and ask a doctor if irritation or rash occurs. These may be signs of a serious condition.

Keep out of reach of children. If swallowed, get medical help or contact a Poison Control Center right away.

Directions

- Place enough product on hands to cover all surfaces. Rub hands together until dry.
- Supervise children under 6 years of age when using this product to avoid swallowing.

Other information:

- Store between 15-30C (59-86F)
- Avoid freezing and excessive heat above 40C (104F)

Inactive ingredients glycerin, hydrogen peroxide, purified water USP

INDICATIONS AND USAGE

Use[s)

Hand Sanitizer to help reduce bacteria that potentially can cause disiease. For use when soap and water are not available.

Directions

Place enough product on hands to cover all surfaces. Rub hands together until dry.
Supervise children under 6 years of age when using this product to avoid swallowing.

PURPOSE

Use[s)

Hand Sanitizer to help reduce bacteria that potentially can cause disiease. For use when soap and water are not available.